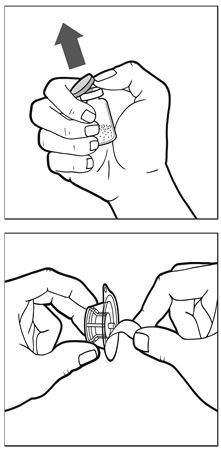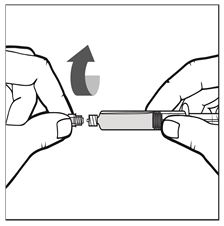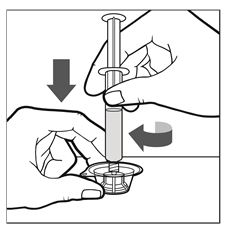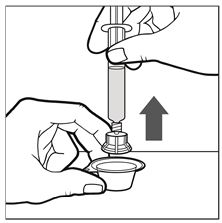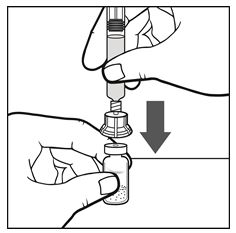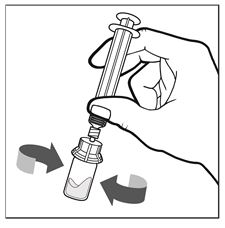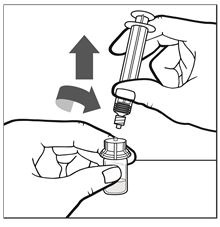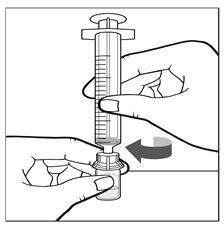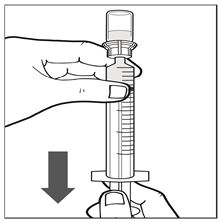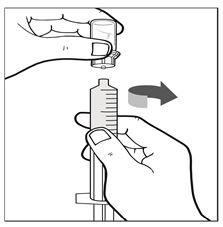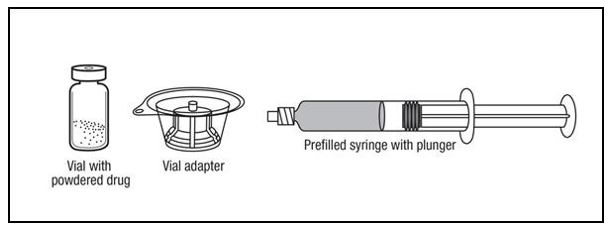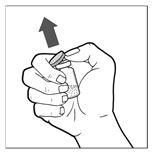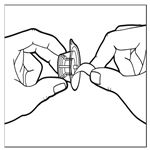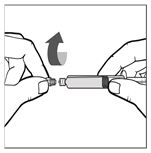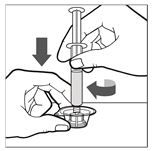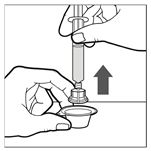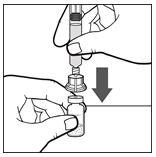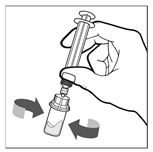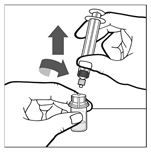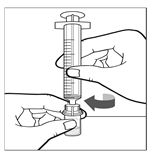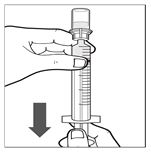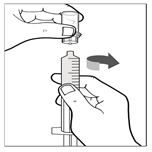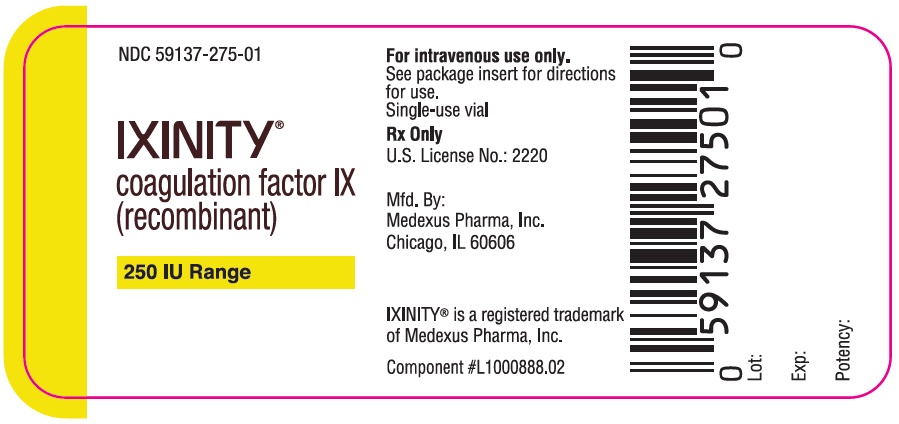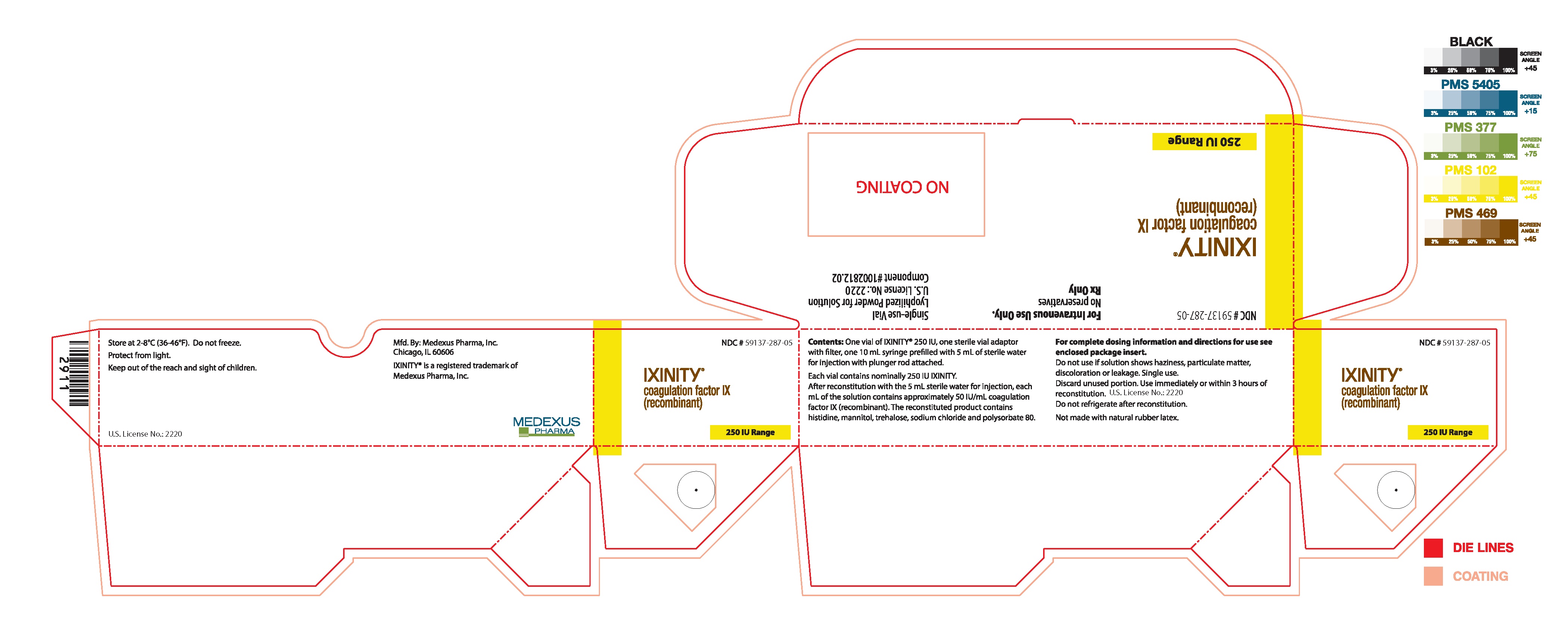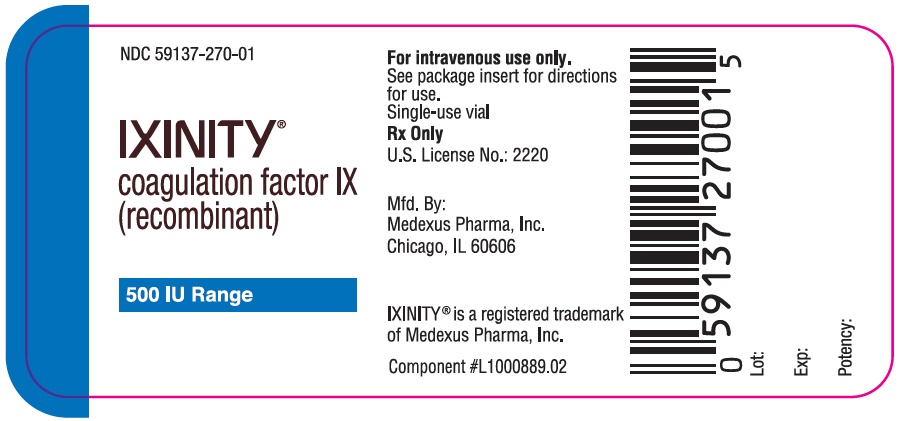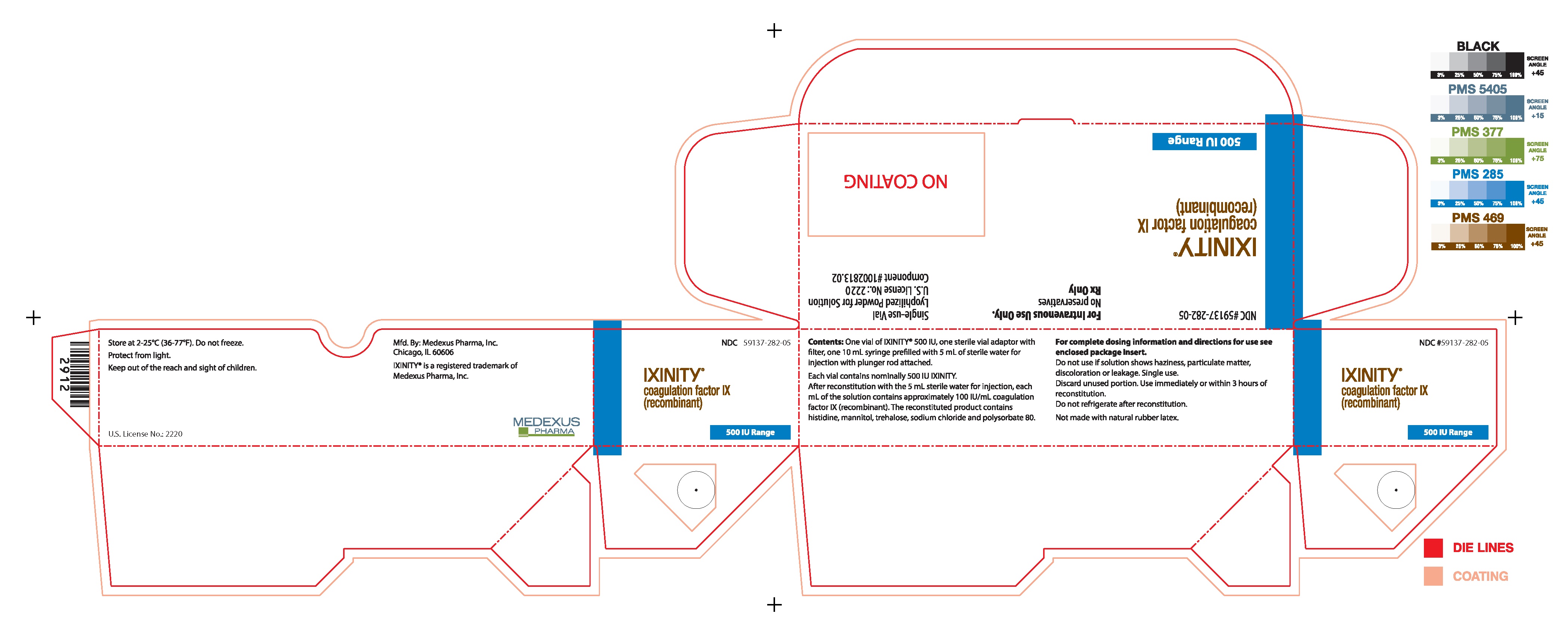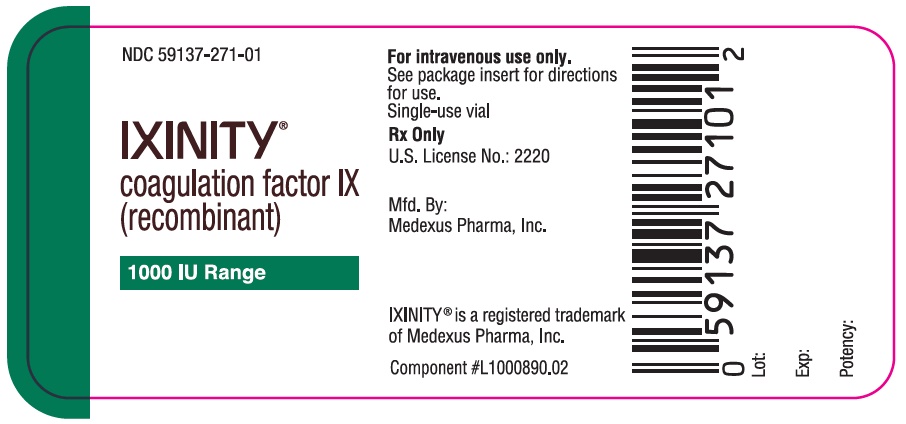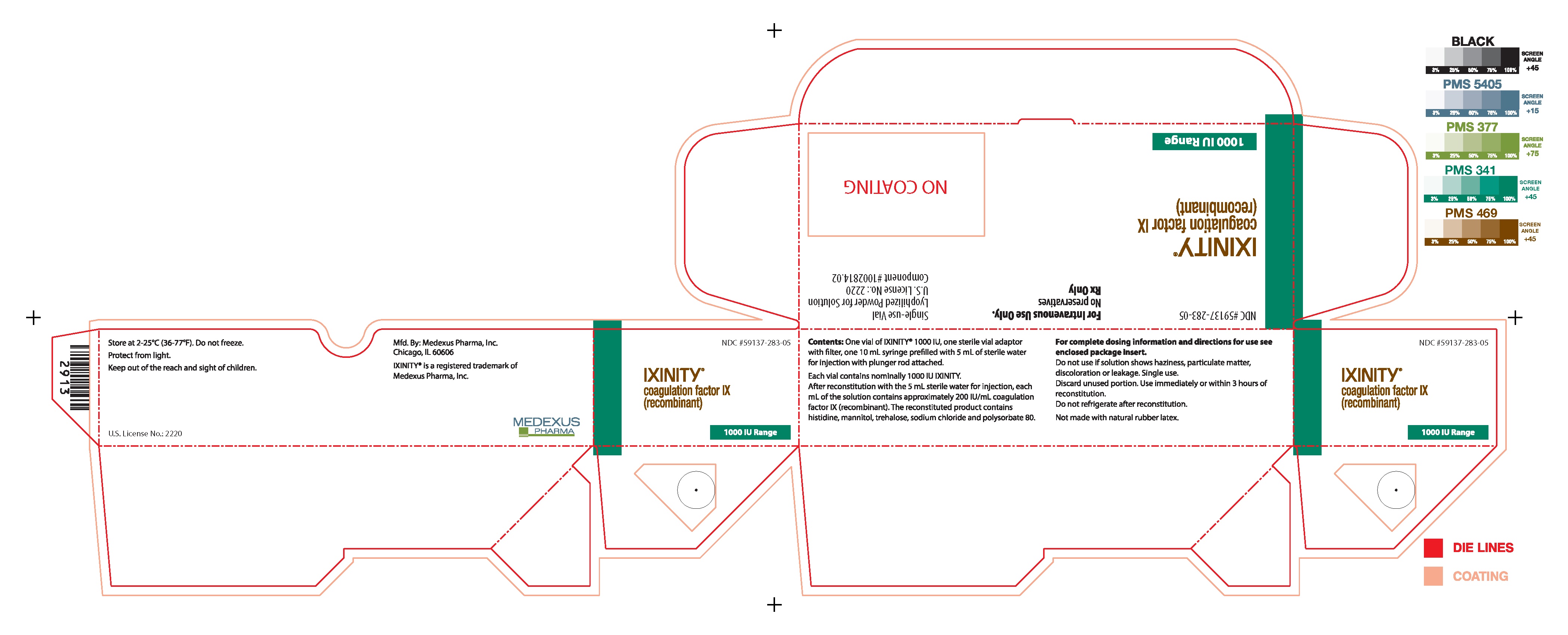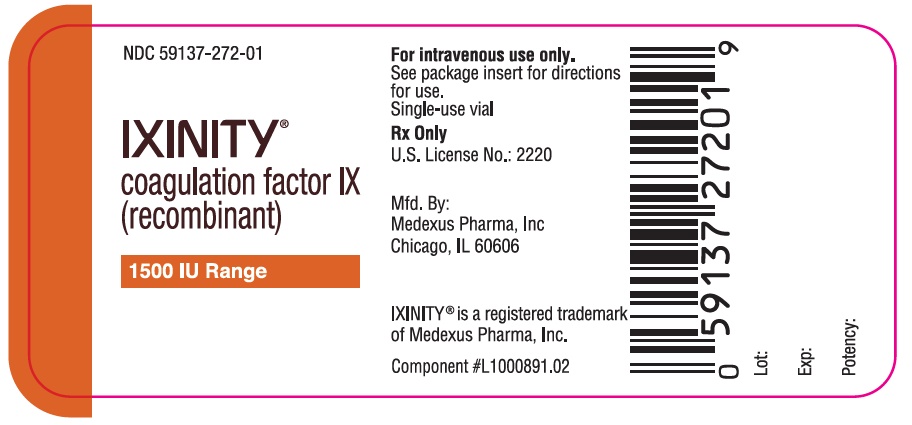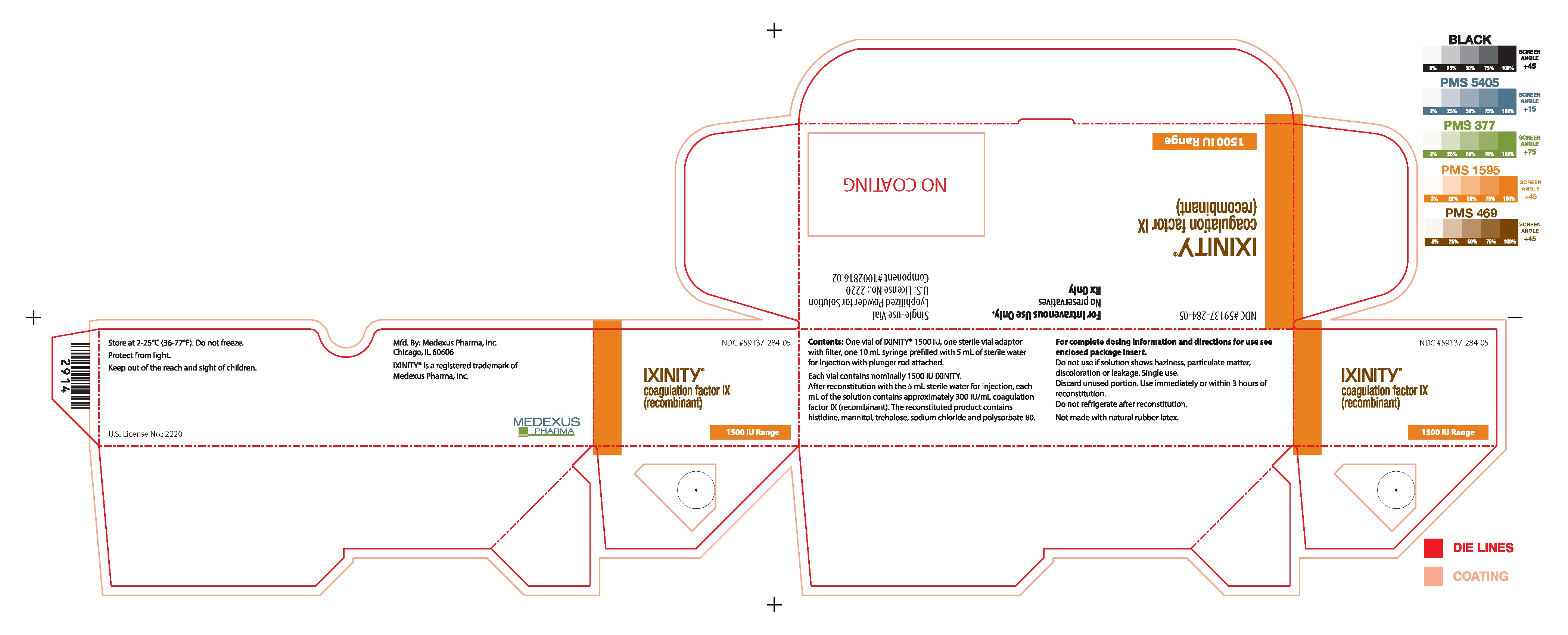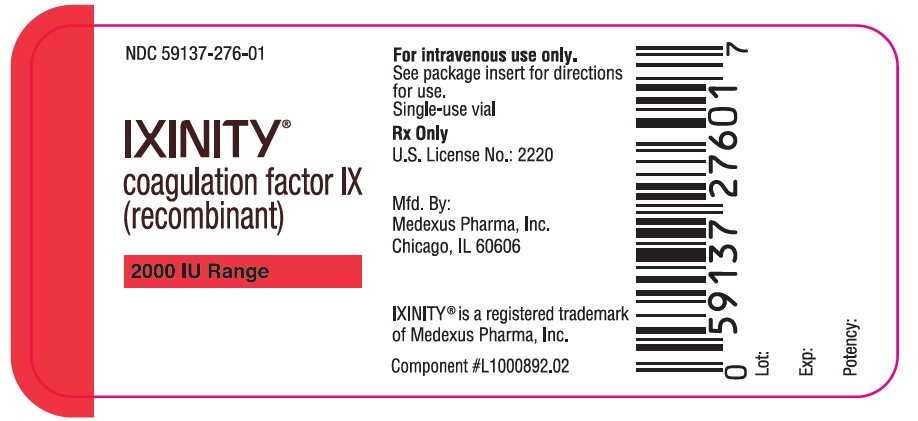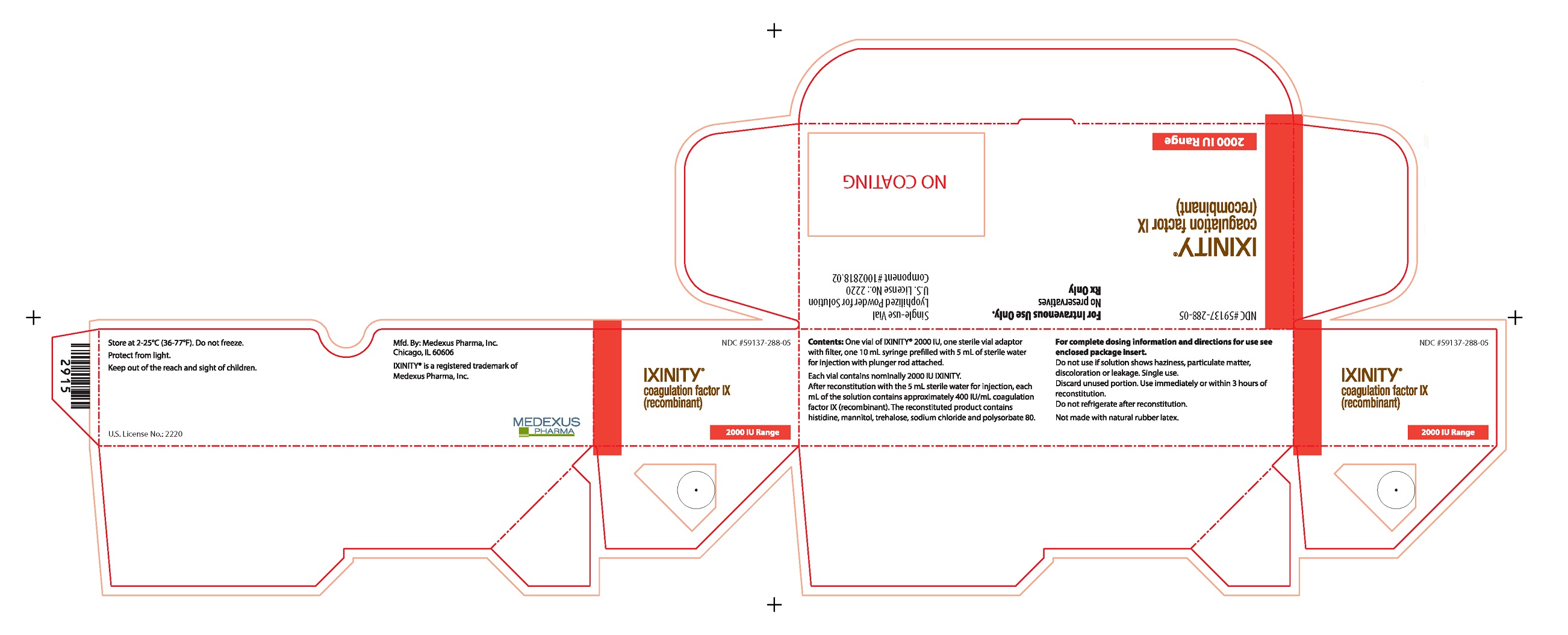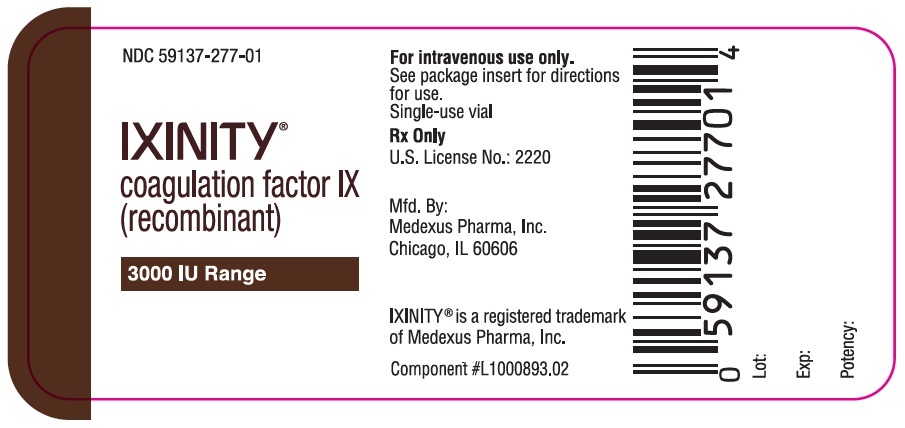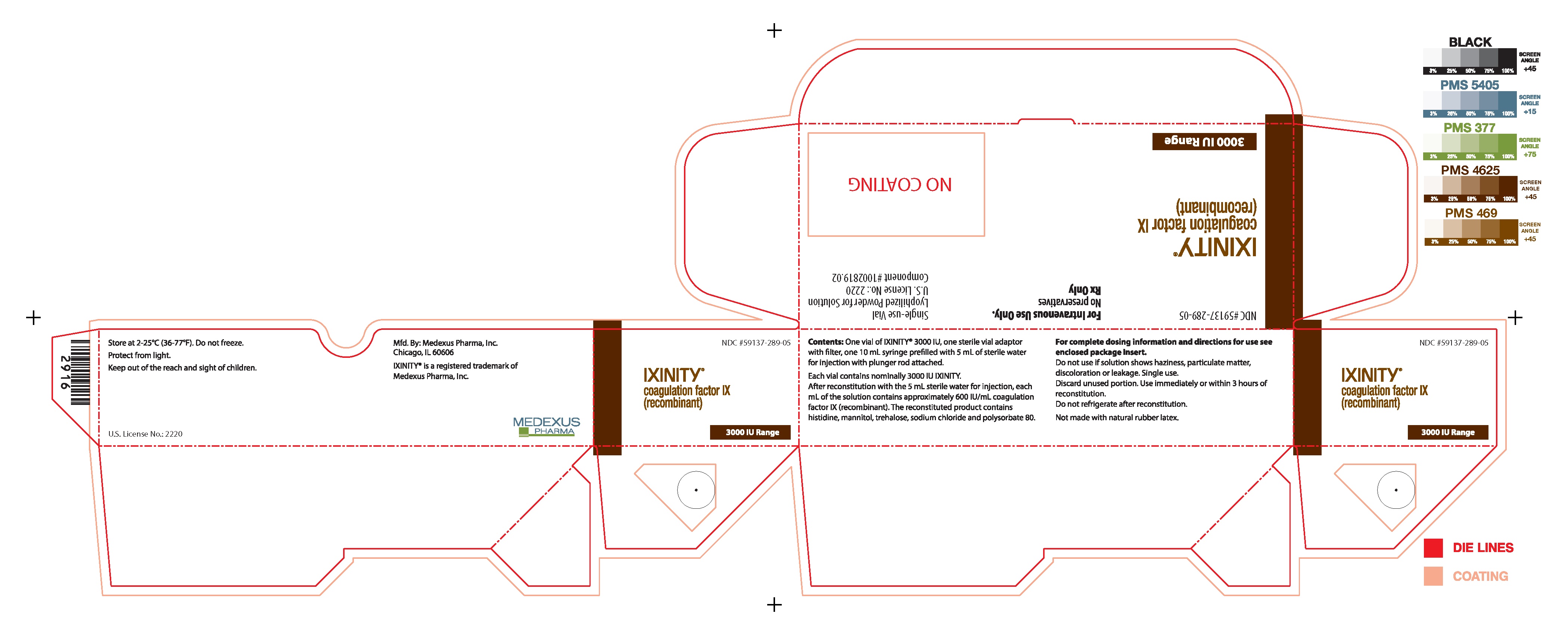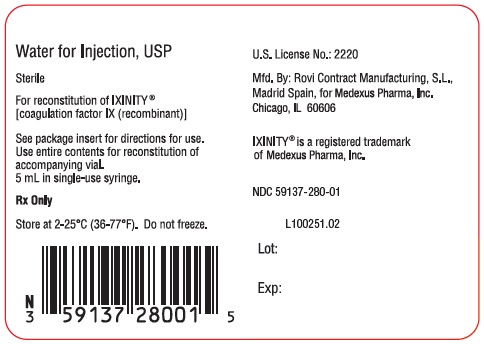 DRUG LABEL: Ixinity
NDC: 59137-287 | Form: KIT | Route: INTRAVENOUS
Manufacturer: Medexus Pharma, Inc.
Category: prescription | Type: HUMAN PRESCRIPTION DRUG LABEL
Date: 20240403

ACTIVE INGREDIENTS: COAGULATION FACTOR IX RECOMBINANT HUMAN 250 [iU]/5 mL
INACTIVE INGREDIENTS: WATER 1 mL/1 mL; HISTIDINE; MANNITOL; TREHALOSE DIHYDRATE; SODIUM CHLORIDE; POLYSORBATE 80

HIGHLIGHTS OF PRESCRIBING INFORMATION

These highlights do not include all the information needed to use IXINITY® safely and effectively. See full prescribing information for IXINITY.
IXINITY [coagulation factor IX (recombinant)]
Lyophilized Powder for Solution for Intravenous Injection
Initial U.S. Approval: 2015

RECENT MAJOR CHANGES

Indications and Usage (1) 03/2024

Dosage and Administration (2.1) 03/2024

1 INDICATIONS AND USAGE

IXINITY, Coagulation Factor IX (Recombinant), is a human blood coagulation factor indicated in adults and children with hemophilia B for:

- On-demand treatment and control of bleeding episodes (1)
- Perioperative management (1)
- Routine prophylaxis to reduce the frequency of bleeding episodes (1)

IXINITY is not indicated for induction of immune tolerance in patients with hemophilia B. (1)

2 DOSAGE AND ADMINISTRATION

For intravenous use after reconstitution only.

On-demand treatment and control of bleeding episodes and perioperative management of bleeding:

- Adolescents/Adults (≥ 12 years of age): One international unit (IU) of IXINITY per kg body weight increases the circulating activity of factor IX by 0.98 IU/dL. (2.1)
- Children (< 12 years of age): One international (IU) of IXINITY per kg body weight increases the circulating activity of factor IX by 0.79 IU/dL. (2.1)

Initial dose:

- Required factor IX units (IU) = body weight (kg) x desired factor IX increase (% of normal or IU/dL) x reciprocal of observed recovery (IU/kg per IU/dL). (2.1)
- The maintenance dose depends on the type of bleed or surgery, the intensity of the hemostatic challenge, and number of days until adequate wound healing is achieved. (2.1)

Routine prophylaxis:

- Adolescents/Adults (≥ 12 years of age): 40 to 70 IU/kg twice weekly. (2.1)
- Children (< 12 years of age): 35 to 75 IU/kg twice weekly. Adjust the dosing regimen (dose or frequency) based on the patient’s clinical response. (2.1)

3 DOSAGE FORMS AND STRENGTHS

IXINITY is available as a lyophilized white or almost white powder, in single-dose glass vials containing nominally 250, 500, 1000, 1500, 2000, or 3000 international units (IU) per vial (3)

4 CONTRAINDICATIONS

Do not use in patients with known hypersensitivity to IXINITY or its excipients, including hamster protein (4)

5 WARNINGS AND PRECAUTIONS

- Hypersensitivity reactions, including anaphylaxis has occurred. Should symptoms occur, discontinue IXINITY and administer appropriate treatment. Patients may also develop hypersensitivity to hamster (CHO) protein, which is present in trace amounts in the product (5.1)
- Development of neutralizing antibodies (inhibitors) to IXINITY may occur. If expected factor IX activity plasma levels are not attained, or if bleeding is not controlled with an appropriate dose, perform an assay that measures factor IX inhibitor concentration (5.2)
- Nephrotic syndrome has been reported following immune tolerance induction with factor IX products in hemophilia B patients with factor IX inhibitors (5.3)
- Thromboembolism has occurred with IXINITY use (5.4)

6 ADVERSE REACTIONS

The most common adverse reaction observed in > 2% of patients in clinical trials was headache (6.1)

To report SUSPECTED ADVERSE REACTIONS, contact Medexus Pharma, Inc. at 1-844-859-6675 or FDA at 1-800-FDA-1088 or www.fda.gov/medwatch.

8 USE IN SPECIFIC POPULATIONS

Pediatric Use: The safety and effectiveness of IXINITY have been established in pediatric patients. Lower recovery, shorter half-life, and higher clearance (based on kg body weight) have been observed in children (< 12 years). Dose adjustment may be needed. (8.4, 12.3)

FULL PRESCRIBING INFORMATION

1 INDICATIONS AND USAGE

IXINITY, Coagulation Factor IX (Recombinant), is a human blood coagulation factor indicated in adults and children with hemophilia B for:

- On-demand treatment and control of bleeding episodes
- Perioperative management
- Routine prophylaxis to reduce the frequency of bleeding episodes

IXINITY is not indicated for induction of immune tolerance in patients with hemophilia B [see Warnings and Precautions (5.3)].

2 DOSAGE AND ADMINISTRATION

For intravenous use after reconstitution only.

2.1 Dose

- Each vial of IXINITY has the recombinant factor IX (rFIX) potency in international units (IU) stated on the vial.
- Dosage and duration of treatment for factor IX products depend on the severity of the factor IX deficiency, the location and extent of bleeding, the patient’s clinical condition, age, and pharmacokinetic parameters of factor IX, such as incremental recovery and half-life.

Initial Dose

Adolescents/Adults ≥ 12 years of age): Calculate the initial dose of IXINITY based on the empirical finding that one international unit (IU) of IXINITY per kg body weight increases the circulating level of factor IX by 0.98 international units/dL (IU/dL) of plasma in adults and children ≥ 12 years of age.

Children (< 12 years of age): Calculate the initial dose of IXINITY based on the empirical finding that one international unit (IU) of IXINITY per kg body weight increases the circulating level of factor IX by 0.79 international units/dL (IU/dL) of plasma in children < 12 years of age.

Initial Dose = body weight (kg) x desired factor IX increase (% of normal or IU/dL)

× reciprocal of observed recovery (IU/kg per IU/dL)

Incremental Recovery in Previously Treated Patients (PTPs)

Base calculation of the dose on the patient’s individual incremental recovery using serial factor IX activity assays, to account for the wide range of inter-individual differences in incremental recovery and the type of aPTT reagent used for the assay. Titrate the dose based on the patient’s clinical response and individual pharmacokinetics, in particular incremental recovery and half-life.

Adolescents/Adults (≥ 12 years of age):

For an incremental recovery of 0.98 IU/dL per IU/kg (0.98% of normal), calculate the dose as follows:

Dose (IU) = body weight (kg) x desired factor IX increase (% of normal or IU/dL)

× 1.02 dL/kg

Examples (assuming patient’s baseline factor IX level is < 1% of normal):

1. A peak of 70% is required in a 60 kg patient. The appropriate dose would be
  (60 kg × 70 IU/dL)/(0.98 IU/dL per IU/kg) = 4286 IU
2. A dose of 4550 international units (IUs) of IXINITY administered to a 70 kg patient should be expected to result in a peak post-infusion factor IX increase of 4550 IU x (0.98 IU/dL per IU/kg)/(70 kg) = 64 IU/dL (approximately 64% of normal)

Children (< 12 years of age):

A lower recovery has been observed in pediatric patients (< 12 years, n=20). For an incremental recovery of 0.79 IU/dL per IU/kg (0.79% of normal), calculate the dose as follows:

Dose (IU) = body weight (kg) x desired factor IX increase (% of normal or IU/dL)

× 1.27 dL/kg

Examples (assuming patient’s baseline factor IX level is < 1% of normal):

1. A peak of 60% is required in a 20 kg patient. The appropriate dose would be (20 kg x 60 IU/dL)/(0.79 IU/dL per IU/kg) = 1519 IU
2. A dose of 500 international units (IUs) of IXINITY administered to a 7 kg patient should be expected to result in a peak post-infusion factor IX increase of 500 IU x (0.79 IU/dL per IU/kg)/(7 kg) = 56 IU/dL (approximately 56% of normal)

- Monitor factor IX activity to ensure that the desired factor IX activity level has been achieved [see Warnings and Precautions (5.5)].
- Titrate doses using factor IX activity and pharmacokinetic parameters such as half-life and incremental recovery, as well as by taking the clinical situation into consideration, to adjust the dose and frequency of repeated infusions as appropriate.
- Factor IX activity measurements in the clinical laboratory may be affected by the type of activated partial thromboplastin time (aPTT) reagent or laboratory standard used [see Warnings and Precautions (5.5)].

On-demand Treatment and Control of Bleeding Episodes and Perioperative Management of Bleeding

Guides for dosing IXINITY in the on-demand treatment and control of bleeding episodes (Table 1) and perioperative management (Table 2) are provided in the tables below. Individual patients may vary in their response to factor IX and may demonstrate different levels of in vivo recovery and different half-lives.

For surgical procedures, initiate treatment with IXINITY early enough pre-operatively to achieve and maintain the desired factor IX level before starting the procedure.

Routine Prophylaxis

For adolescents/ adults ≥ 12 years of age the recommended dose for previously treated patients (PTPs) is 40 to 70 IU/kg twice weekly.

For children < 12 years of age the recommended dose for previously treated patients (PTPs) is 35 to 75 IU/kg twice weekly. Children (<12 years) have lower recovery, shorter half-life and higher clearance (based on per kg body weight) as compared to adolescents and adults. Adjust the dosing regimen (dose or frequency) based on the patient's clinical response. Adjust the dose based on the individual patient’s age, bleeding pattern, and physical activity.

Table 1 Dosing for On-demand Treatment and Control of Bleeding Episodes
Type of Bleeding Episode | Desired Peak Factor IX Level (% of normal or IU/dL) | Dosing Interval (hours) | Duration of therapy (days)
Minor Early bleeds: uncomplicated hemarthroses and superficial muscle (except iliopsoas) with no neurovascular compromise, other soft tissue | 30-60 | 24 | 1-3, until healing is achieved
Moderate Hemarthrosis of longer duration, recurrent hemarthrosis, mucous membranes, deep lacerations, hematuria | 40-60 | 24 | 2-7, until healing is achieved
Major or Life Threatening Iliopsoas, deep muscle with neurovascular injury, substantial blood loss, CNS, pharyngeal, retropharyngeal, retroperitoneal | 60-100 | 12-24 | 2-14, until healing is achieved
Adapted from Srivastava et al. 2013 (1).

Table 2 Dosing for Perioperative Management
Type of Surgery | Desired Peak Factor IX Level (% of normal or IU/dL) | Dosing Interval (hours) | Duration of therapy (days)
Minor (including uncomplicated dental extractions)
Pre-op | 50-80
Post-op | 30-80 | 24 | 1-5, depending on type of procedure
Major
Pre-op | 60-80
Post-op | 40-60 30-50 20-40 | 8-24 | 1-3 4-6 7-14
Adapted from Srivastava et al. 2013 (1).

2.2 Preparation and Reconstitution

The procedures below are provided as general recommendations for the preparation and reconstitution of IXINITY.

Before starting reconstitution and administration you will need the following items that are included in each kit of IXINITY:

- One (or more) vial(s) of IXINITY 250, 500, 1000, 1500, 2000, or 3000 IU powder
- One (or more) 10 mL syringe(s), pre-filled with 5 mL of Sterile Water for Injection (pre-filled syringe) with plunger rod attached
- One sterile vial adapter with filter

In addition, you will need the following items that are not included in the kit:

- One sterile LUER-LOK™ syringe (administration syringe); additional or larger syringes may be required if pooling multiple vials
- Sterile alcohol swabs
- Sterile infusion set
- Sterile gauze pad
- Sterile bandage

Always work on a clean surface and wash your hands before performing the following procedures:

1. Use aseptic technique during reconstitution procedure.
2. Allow IXINITY and the pre-filled syringe to reach room temperature before use.
3. Remove cap from the vial (See Figure A). Peel back the cover of the vial adapter package (leave the vial adapter in the package).
  Figure A
4. Place the administration syringe, if using, and vial adapter on a clean flat work surface.
5. Twist off the cap of the pre-filled syringe and place it on the clean flat surface (See Figure B).
  Figure B
6. Wipe the top of the IXINITY vial with an alcohol swab (or similar germicidal solution) and allow it to dry. Place on a clean, flat surface.
7. Firmly hold the package containing the vial adapter on a clean, flat surface. Connect the pre-filled syringe to the vial adapter by pushing the syringe tip down onto the LUER-LOK in the center of the vial adapter, and screw until the syringe is secured (See Figure C).
  Figure C
8. Carefully lift up the combined syringe-and-vial-adapter and remove it from the plastic package (See Figure D).
  Figure D
9. With one hand, continue to hold the combined syringe-and-vial-adapter. With the other hand, hold the IXINITY vial tightly on a clean, flat surface. In a continuous motion, place the vial adapter over the IXINITY vial; firmly push the filter spike of the vial adapter through the center of IXINITY vial’s rubber circle until the clear plastic cap snaps onto the IXINITY vial (See Figure E). Push the plunger down to complete the transfer of all liquid from the syringe to the IXINITY vial.
  Figure E
10. With the syringe and the vial still attached, gently swirl, in a circular motion, the IXINITY vial until the product is fully dissolved/reconstituted (See Figure F).
  Figure F
11. Remove the pre-filled syringe (now empty) from the vial adapter by turning it counterclockwise until it is completely detached (See Figure G).
  Figure G
12. Remove the administration syringe from its packaging.
13. Leave the vial adapter attached to the vial and attach the administration syringe to the vial adapter by turning clockwise until it is securely attached (See Figure H).
  Figure H
14. Keeping the administration syringe plunger pressed, turn the IXINITY vial upside down. Draw the solution from the vial through the filter spike in the vial adapter by pulling the plunger back slowly until all solution is transferred into the administration syringe (See Figure I).
  Figure I
15. Keep the administration syringe plunger facing downwards and prevent it from moving. With one hand hold the vial-and-vial-adapter, and with the other hand firmly grasp the barrel of the administration syringe and unscrew the syringe from the vial adapter (See Figure J).
  Figure J
16. If only dosing with a single vial, proceed to administer IXINITY via intravenous infusion; otherwise proceed to Pooling Instructions.

POOLING INSTRUCTIONS

1. If two or more vials are required to achieve the required dose, remove the pre-filled syringe from the vial adapter on the reconstituted second vial by turning it counterclockwise until it is completely detached.
2. Leave the vial adapter attached to the vial and attach the administration syringe containing the reconstituted IXINITY from the first vial by turning it clockwise until it is securely in place.
3. Turn the IXINITY vial upside down and slowly pull on the plunger rod to draw the solution into the administration syringe (see Figure I).
4. Continue with remaining vials, if required. Once pooling is complete, proceed to administer IXINITY via intravenous infusion.
  - After reconstitution of the lyophilized powder, all dosage strengths should yield a clear, colorless solution without visible particles. Discard if visible particulate matter or discoloration is observed.
  - Infuse reconstituted solution immediately or within 3 hours of storage at room temperature after reconstitution. Do not refrigerate after reconstitution.
  - Do not touch the syringe tip or the inside of the cap. Place the syringe containing the IXINITY solution on the clean surface, making sure that the tip does not touch anything.

2.3 Administration

For intravenous use after reconstitution only.

1. Inspect parenteral drug products visually for particulate matter and discoloration prior to administration, whenever solution and container permit.
2. Do not mix IXINITY with other medicinal products for infusion.
3. Attach the administration syringe containing the reconstituted IXINITY solution to a sterile infusion set.
4. Adapt the infusion rate to the comfort level of each patient, not exceeding 10 mL per minute.
5. Record the name and batch number of the product in the patient record.

Dispose of any unused product or waste material in accordance with local requirements.

3 DOSAGE FORMS AND STRENGTHS

IXINITY is available as a lyophilized white or almost white powder, in single-dose glass vials containing nominally 250, 500, 1000, 1500, 2000, or 3000 IU per vial.

4 CONTRAINDICATIONS

IXINITY is contraindicated in patients who have known hypersensitivity to IXINITY or its excipients, including hamster protein [see Warnings and Precautions (5.1)].

5 WARNINGS AND PRECAUTIONS

5.1 Hypersensitivity Reactions

Hypersensitivity reactions, including anaphylaxis, has occurred with IXINITY. Signs of allergic reactions, which can progress to anaphylaxis, include urticaria, angioedema, chest or throat tightness, hypotension, lethargy, nausea, vomiting, dysphagia, paresthesia, restlessness, wheezing and dyspnea. Immediately discontinue administration and initiate appropriate treatment if allergic or anaphylactic-type reactions occur. In case of severe allergic reactions, consider alternative hemostatic measures.

There are literature reports of allergic reactions occurring in close temporal association with the development of factor IX inhibitors.

IXINITY contains trace amounts of Chinese hamster ovary (CHO) proteins. Patients treated with this product may develop hypersensitivity to CHO proteins.

5.2 Neutralizing Antibodies

Development of neutralizing antibodies (inhibitors) to IXINITY may occur. If expected factor IX activity plasma levels are not attained, or if bleeding is not controlled as expected with the calculated dose, perform an assay that measures factor IX inhibitor concentration [see Warnings and Precautions (5.5)].

Patients with factor IX inhibitors are at an increased risk of severe hypersensitivity reactions or anaphylaxis if re-exposed to IXINITY.

5.3 Nephrotic Syndrome

Nephrotic syndrome may occur with IXINITY. Nephrotic syndrome has been reported following attempted immune tolerance induction in hemophilia B patients with factor IX inhibitors and a history of allergic reactions.

5.4 Thromboembolism

Thromboembolism has occurred with IXINITY use. One thrombotic event of deep vein thrombosis was reported in an adult female over 45 years of age from post-marketing experience. Because of the potential risk for thromboembolism with the use of factor IX products, monitor for early signs of thromboembolism and consumptive coagulopathy when administering IXINITY to patients with liver disease, fibrinolysis, peri-operative status, or risk for thromboembolic events or disseminated intravascular coagulation.

5.5 Monitoring Laboratory Tests

- Monitor patients for factor IX activity levels with the one-stage clotting assay to confirm that adequate factor IX levels have been achieved and maintained, when clinically indicated. Factor IX results can be affected by the type of aPTT reagent used [see Dosage and Administration (2.1)].
- Monitor patients for the development of inhibitors if expected factor IX activity plasma levels are not attained, or if bleeding is not controlled with the recommended dose of IXINITY. Assays used to determine if factor IX inhibitor is present should be titered in Bethesda Units (BUs).

6 ADVERSE REACTIONS

The most common adverse reaction (> 2%) reported in clinical trials was headache.

6.1 Clinical Trials Experience

Because clinical trials are conducted under widely varying conditions, adverse reaction rates observed in the clinical trials of a drug cannot be directly compared to rates in the clinical trials of another drug and may not reflect the rates observed in clinical practice.

A total of 15 adverse reactions were reported following IXINITY administration among 7 of the 98 subjects who received at least one dose of IXINITY in trials of previously treated patients (PTPs), which included 11 subjects 12 - 18 years of age and 21 subjects < 12 years of age. A total of 12,952 infusions of IXINITY were administered to the 98 subjects. The adverse reactions that were assessed as probably or possibly related to study drug are provided in the table below.

Table 3 Summary of Adverse Reactions
MedDRA Standard System Organ Class | Adverse Reaction | Number of Events | Number of Subjects (n = 98) (%)
Congenital, familial and genetic disorders | Hemophilia (i.e., lack of efficacy) | 1 | 1 (1.0%)
General disorders and administration site conditions | Asthenia | 1 | 1 (1.0%)
General disorders and administration site conditions | Injection site discomfort | 1 | 1 (1.0%)
Immune System Disorders | Hypersensitivity | 1 | 1 (1.0%)
Infections and infestations | Influenza | 1 | 1 (1.0%)
Nervous system disorders | Headache | 5 | 2 (2.0%)
Nervous system disorders | Dysgeusia | 1 | 1 (1.0%)
Nervous system disorders | Lethargy | 1 | 1 (1.0%)
Psychiatric disorders | Apathy | 1 | 1 (1.0%)
Psychiatric disorders | Depression | 1 | 1 (1.0%)
Skin and subcutaneous tissue disorders | Rash pruritic | 1 | 1 (1.0%)

6.2 Postmarketing Experience

The following adverse reactions have been identified during post approval use of IXINITY.

Because these reactions are reported voluntarily from a population of uncertain size, it is not always possible to reliably estimate their frequency or establish a causal relationship to drug exposure.

Immune System Disorders: Anaphylaxis

Vascular Disorders: Deep vein thrombosis

The following class adverse reactions have been seen with another recombinant factor IX: inadequate factor IX recovery, inhibitor development, angioedema, hypotension, and thrombosis.

8 USE IN SPECIFIC POPULATIONS

8.1 Pregnancy

Risk Summary

There are no data with IXINITY use in pregnant women to inform a drug-associated risk. Animal reproduction studies have not been conducted with IXINITY.

In the U.S. general population, the estimated background risk of major birth defect and miscarriage in clinically recognized pregnancies is 2-4% and 15-20%, respectively.

8.2 Lactation

Risk Summary

There is no information regarding the presence of IXINITY in human milk, the effect on the breastfed infant, or the effects on milk production. The developmental and health benefits of breastfeeding should be considered along with the mother’s clinical need for IXINITY and any potential adverse effects on the breastfed infant from IXINITY or from the underlying maternal condition.

8.4 Pediatric Use

The safety, efficacy, and pharmacokinetics of IXINITY have been evaluated in previously treated pediatric patients (PTP). Subjects received twice or once weekly prophylaxis treatment (four subjects were prescribed once a week treatment, 17 were prescribed twice a week treatment) with IXINITY for a mean of 158.7 exposure days [see Clinical Studies (14)].

Compared to adolescents and adults (≥ 12 years old), children (< 12 years old) showed higher Factor IX body weight-adjusted clearance, shorter half-life, and lower recovery. Adjustment in dose or dosing frequency may be needed [see Dosage and Administration (2.1) and Clinical Pharmacology (12.3)].

There were no inhibitors detected [see Clinical Pharmacology (12.6)]. One patient in the pediatric study had an adverse reaction of hypersensitivity resulting in withdrawal from the study. No new safety concerns were identified in the pediatric trial [see Adverse Reactions (6.1)].

8.5 Geriatric Use

Clinical studies of IXINITY did not include subjects aged 65 and over. It is not known whether elderly patients respond differently than younger patients. Individualize dose selection for elderly patients [see Dosage and Administration (2.1)].

11 DESCRIPTION

IXINITY [coagulation factor IX (recombinant)] is a purified protein that has 415 amino acids. It has an amino acid sequence that is comparable to the Thr148 allelic form of plasma-derived factor IX. Coagulation factor IX (recombinant) is a single-chain glycoprotein with a molecular mass of about 55,000 Dalton that is secreted by a genetically engineered mammalian cell line derived from Chinese hamster ovary (CHO) cells. No human or animal proteins are added during any stage of manufacturing or formulation of IXINITY. The CHO cell line secretes recombinant factor IX into a defined cell culture medium that does not contain hormones. The recombinant factor IX is purified by a chromatography purification process. The process includes three validated steps for virus inactivation and removal, namely, solvent/detergent treatment, a chromatographic step, and nanofiltration. The process also includes a validated step to reduce the presence of CHO proteins in the final drug product.

IXINITY is formulated as a sterile, nonpyrogenic lyophilized powder to be reconstituted with Sterile Water for Injection for intravenous administration. It does not contain any preservatives and is available in single-dose vials containing the labeled amount of factor IX activity, expressed in international units (IU). Each vial contains nominally 250, 500, 1000, 1500, 2000, or 3000 IU of recombinant coagulation factor IX. After reconstitution of the lyophilized powder, all dosage strengths yield a clear, colorless solution. The concentrations of excipients are:

Excipient | Concentration
Histidine | 10 mM
Mannitol | 3%
Trehalose Dihydrate | 1%
Sodium Chloride | 66 mM
Polysorbate 80 | 0.0075%

12 CLINICAL PHARMACOLOGY

12.1 Mechanism of Action

Hemophilia B is a sex-linked hereditary disorder of blood coagulation caused by a deficiency in factor IX and results in bleeding into joints, muscles or internal organs, either spontaneously or as a result of accidental or surgical trauma. Treatment with IXINITY replaces factor IX, thereby enabling a temporary correction of the factor deficiency and correction of the bleeding tendencies.

12.2 Pharmacodynamics

The administration of IXINITY increases plasma levels of factor IX and can temporarily correct the coagulation defect in these patients, as reflected by decrease in the aPTT.

12.3 Pharmacokinetics

PTPs ≥ 12 years of age

Pharmacokinetic studies with IXINITY were conducted in 32 previously treated patients (PTPs) ≥ 12 years of age with severe to moderately severe hemophilia B (factor IX ≤ 2 IU/dL). Intravenous administration of 75 ± 5 IU/kg of IXINITY to 32 PTPs showed an initial recovery ranging from 51 to 113 IU/dL (median 70 IU/dL). The results of pharmacokinetic studies are summarized below in Table 4.

Table 4 Pharmacokinetic Parameters for IXINITY PTPs ≥ 12 Years of Age (n = 32)
Parameters | Mean (± SD) (Range)
AUC0–∞ (IU/dL/hr) | 1573 (± 451) (862-2643)
Incremental Recovery (IU/dL per IU/kg) | 0.98 (± 0.21) (0.67-1.50)
Terminal Half-life (hours) | 24 (± 7) (13-43)
Cmax (IU/dL) | 73 (± 17) (51-113)
Mean Residence Time (hours) | 32 (± 6) (19-47)
VDss (mL/kg) | 175 (± 57) (102-314)
Clearance [mL/(kg·hr)] | 5.1 (± 1.3) (2.8-7.7)

Pharmacokinetic parameters were re-assessed in a subset of 14 subjects after routine treatment with IXINITY for a median of 5.8 months (range 3.1 to 18.6 months) as summarized in Table 5 below.

Table 5 Pharmacokinetic Parameters for IXINITY Following Repeat-Dosing PTPs ≥ 12 Years of Age (n = 14)
Parameters | Initial Mean (± SD) | Repeat-Dosing PK Mean (± SD)
AUC0–∞ (IU/dL/hr) | 1438 (± 409) | 1530 (± 435)
Incremental Recovery (IU/dL per IU/kg) | 0.96 (± 0.22) | 0.95 (± 0.18)
Terminal Half-life (hours) | 24 (± 7) | 24 (± 6)
Cmax (IU/dL) | 73 (± 16) | 73 (± 15)
Mean Residence Time (hours) | 30 (± 6) | 31 (± 5)
VDss (mL/kg) | 193 (± 62) | 185 (± 70)
Clearance [mL/(kg·hr)] | 5.6 ± (1.3) | 5.3 (± 1.5)

Repeat dosing did not impact the pharmacokinetics of IXINITY.

The PK data were divided into two subgroups of subjects with a BMI ≤ 30 (n = 26) or BMI > 30 (n = 6). The AUC(0-∞) and Cmax values of IXINITY were 40% and 34% higher, respectively, in subjects with BMI > 30.

PTPs <12 years of age

Pharmacokinetics were evaluated in 20 previously treated patients (PTPs) < 12 years of age with severe to moderately severe hemophilia B (factor IX ≤ 2 IU/dL).

Following a single intravenous administration of 75 ± 5 IU/kg of IXINITY, an initial recovery ranged from 44 to 109 IU/dL (median 77 IU/dL). Pediatric patients < 12 years of age showed higher clearance, shorter half-life, and lower incremental recovery compared to adults and adolescents (≥ 12 years old). The results of pharmacokinetic studies are summarized below in Table 6.

Table 6 Pharmacokinetic Parameters for PTPs <12 Years of Age Following 75 ± 5 IU/kg of IXINITY (n=20)
Parameters | < 6 years N=10a Mean (± SD) | 6 to < 12 years N=10b Mean (± SD) | All subjects < 12 years N=20c Mean (± SD)
AUC0–∞ (IU/dL/hr) | 1118 (± 307) | 1232 (± 81.7) | 1170 (± 231)
Incremental Recovery (IU/dL per IU/kg) | 0.73 (± 0.15) | 0.85 (± 0.15) | 0.79 (± 0.16)
Terminal Half-life (hours) | 15.9 (± 1.4) | 16.8 (± 2.8) | 16.3 (± 2.2)
Cmax (IU/dL) | 56.4 (± 13.7) | 63.7 (± 9.86) | 60.1 (± 12.2)
Mean Residence Time (hours) | 19.9 (± 2.48) | 20.0 (± 2.87) | 20.0 (± 2.53)
VDss (mL/kg) | 144 (± 36.7) | 123 (± 18.9) | 134 (± 30.6)
Clearance [mL/(kg·hr)] | 7.3 (± 1.9) | 6.1 (± 0.5) | 6.8 (± 1.5)
a n=6 for t1/2, AUC0-∞, MRT, CL, and Vdss
b n=6 for t1/2 and n=5 for AUC0-∞, MRT, CL, and Vdss
c n=12 for t1/2 and n=11 for AUC0-∞, MRT, CL, and Vdss

12.6 Immunogenicity

The observed incidence of anti-drug antibodies is highly dependent on the sensitivity and specificity of the assay. Differences in assay methods preclude meaningful comparisons of the incidence of anti-drug antibodies in the studies described below with the incidence of anti-drug antibodies in other studies, including those of IXINITY or of other factor IX products.

Routine Prophylaxis

PTPs ≥ 12 years of age

All subjects participating in the clinical trial were monitored for inhibitory and non-inhibitory antibodies to factor IX and antibodies for CHO cell proteins (CHOP) at the following time points; pre-infusion, after the first five exposure days, and then every three months thereafter.

No subjects developed inhibitors to factor IX, including 55 subjects with more than 50 exposure days and 45 of those subjects with more than 100 exposure days. Non-inhibitory factor IX binding antibodies were detected in 30% (23/77) of subjects, including five subjects positive at baseline. In three of the subjects, the non-inhibitory factor IX antibodies were persistent, while in the remainder the antibodies were sporadic and non-persistent.

Antibodies against CHOP were observed in 29% (20/68) of subjects. The manufacturing process for IXINITY was modified to include an additional step to ensure increased clearance of CHOP to address the anti-CHOP response seen in clinical trials. Subjects who transitioned to the modified IXINITY for at least three months (n = 17), anti-CHOP antibodies remained negative (n = 10), stable/nonspecific assay binding (n = 5) or declined (n = 2) after the transition.

PTPs <12 years of age

All subjects participating in the clinical trial were monitored for inhibitory and non-inhibitory antibodies to factor IX and antibodies for CHOP at the following time points; at screening, pre-infusion, then at exposure day 5, 12, 25, 50, 75, 100, and then every three months thereafter.

No subjects developed inhibitors to factor IX, including 19 subjects with more than 50 exposure days and 16 of those subjects with more than 100 exposure days. Non-inhibitory factor IX binding antibodies were detected in 14% (3/21) of subjects, including two subjects positive at baseline; in one subject, the non-inhibitory factor IX antibodies were persistent.

Anti-CHOP antibodies were detected in 14% (3/21) of subjects; in one subject, the anti-CHOP antibodies were persistent. There was no correlation between the three subjects who developed non-inhibitory anti-factor IX antibodies and the three subjects who tested positive for anti-CHOP antibodies.

Effects of non-inhibitory anti-factor IX antibodies and anti-CHOP antibodies

Detection of non-inhibitory anti-factor IX antibodies or anti-CHOP antibodies has been reported following administration of other factor IX products or other recombinant coagulation factor products produced in CHO cells. No adverse events were associated with non-inhibitory anti-factor IX antibodies or anti-CHOP antibodies. However, the effect of these antibodies on the pharmacokinetics and effectiveness of IXINITY is unknown.

13 NONCLINICAL TOXICOLOGY

13.1 Carcinogenesis, Mutagenesis, Impairment of Fertility

No macroscopic or microscopic pathologies in reproductive organs were observed in repeated dose toxicity studies of IXINITY in animals. Animal studies regarding impairment of fertility were not conducted.

No nonclinical investigations of genotoxicity, carcinogenicity, or toxicity to reproduction and development have been conducted with IXINITY.

14 CLINICAL STUDIES

Routine Prophylaxis

PTPs ≥ 12 years of age

The efficacy of IXINITY was evaluated in a prospective, open-label, uncontrolled multicenter study in which a total of 77 subjects (76 male, 1 female carrier in surgery study) were exposed to IXINITY for treatment of hemophilia B or for perioperative management. All male subjects either had severe or moderately severe (factor IX level ≤ 2 IU/dL) hemophilia B, or had factor IX levels between 2-8 IU/dL and clinically severe hemophilia B with recurrent hemarthroses and required surgery (n = 3 in surgery study, one continued to treatment phase). Previously treated patients (PTPs) were defined as patients with a minimum of 150 exposures to another factor IX preparation. Of the 77 subjects, 68 PTPs between 7 and 64 years of age received IXINITY either as routine prophylaxis or on-demand treatment. Routine prophylaxis treatment was defined as PTPs who received a starting dose of 40-70 international units (IU) per kg twice weekly. Excluded from the study were patients with a history of a detectable factor IX inhibitor (≥ 0.6 BU), a history of hypersensitivity reactions following exposure to factor IX-containing products, a known allergic reaction to hamster proteins, evidence of severe liver impairment, evidence of impaired renal function, CD4 count < 400 cells/mm^3, or any coagulation defect other than hemophilia B. In addition, there was a prospective, open-label, uncontrolled, multicenter substudy where 17 subjects (16 male, 1 female carrier) underwent surgeries (19 major procedures in males) receiving IXINITY for perioperative management; some of the surgery subjects also participated in the treatment trial.

Of the 68 PTPs in the treatment group, subjects were primarily prescribed a routine prophylaxis (n = 58) or an on-demand regimen (n = 9); one subject was not assigned a regimen. Subjects were allowed to switch regimens during the course of the study. As a result, 61 subjects were treated at some point with routine prophylaxis treatment and 12 were treated at some point with an on-demand regimen. Subjects in the routine prophylaxis therapy group received mean intravenous doses of 55 ± 12.8 IU/kg of IXINITY twice weekly. Subjects in the on-demand therapy group received mean doses of 60 ± 18.2 IU/kg (median 59.3, interquartile range 49.9, 71.8) for bleeding episodes. The mean number of exposure days (ED) was 138.2 (median 127.5), including 45 subjects with ≥ 100 ED and 55 subjects with ≥ 50 ED. Median duration on study for the on-demand group was 14.1 months (range 2.3-36.9).

Annualized bleeding rates for PTPs ≥12 years of age in prophylaxis arm are summarized in Table 7.

Table 7: Efficacy of Prophylaxis with IXINITY (N=61) for subjects ≥ 12 years of age
Total ABR
Mean ± SD | 3.55 ± 7.19
Median (Q1, Q3)a | 1.52 (0;3.47)
Spontaneous ABR
Mean ± SD | 1.07± 3.06
Median (Q1, Q3)a | 0.00 (0;1.22)
Subjects with zero bleeding episodes
n (%) | 19 (31.1%)
aThe lower quartile, or first quartile (Q1) is the value under which 25% of data points are found when arranged in increasing order. The upper quartile, or third quartile (Q3), is the value under which 75% of data points are found when arranged in increasing order.

PTP < 12 years of age

The PK, safety and efficacy of IXINITY for treatment of hemophilia B was evaluated in a prospective multi-center, multi-country study of 21 previously treated patients (PTPs) (10 subjects < 6 years of age and 11 subjects 6 to < 12 years of age). PTP were defined as patients who were exposed to a factor IX containing product for ≥ 50 exposure days (ED). All subjects had severe to moderately severe (factor ≤ 2%). Subjects with history of hypersensitivity reactions following exposure to factor IX-containing products, a known allergic reaction to hamster proteins, evidence of severe liver impairment, evidence of impaired renal function, CD4 count < 400 cells/mm^3, or any coagulation defect other than hemophilia B, evidence of thrombotic disease, fibrinolysis, or disseminated intravascular coagulation (DIC) were excluded from the trial.

Subjects received IXINITY prophylaxis once to twice weekly, the recommended dose range was 35 – 75 IU/kg. Subjects < 6 years received a mean intravenous dose of 58 (45-72) ± 8.9 IU/kg and subjects 6 to < 12 received a mean intravenous dose of 52 (46-60) ± 11.6 IU/kg. Twenty-one subjects completed the PK analysis, and 19 subjects completed a minimum of 50 ED. The mean number of ED was 159 (median 163), including 16 subjects with ≥ 100 ED and 7 subjects with ≥ 200 ED.

Annualized bleeding rates for PTPs <12 years of age are summarized in Table 8.

Table 8: Efficacy of Prophylaxis with IXINITY (N=21) for subjects <12 years of age
Total ABR
Mean ± SD | 2.34 ± 4.23
Median (Q1, Q3)a | 0.86 (0;1.96)
Spontaneous ABR
Mean ± SD | 0.63 ± 1.26
Median (Q1, Q3)a | 0.00 (0;0.85)
Subjects with zero bleeding episodes
n (%) | 7 (33.3%)
aThe lower quartile, or first quartile (Q1) is the value under which 25% of data points are found when arranged in increasing order. The upper quartile, or third quartile (Q3), is the value under which 75% of data points are found when arranged in increasing order.

Control of Bleeding Episodes

PTPs ≥ 12 years of age

A total of 508 bleeding episodes were treated with IXINITY, of which 286 bleeds were recorded for subjects treated with the routine prophylaxis treatment regimen and 222 with the on-demand regimen. Bleeding resolved in 360 episodes (70.9%) after a single infusion of IXINITY and in 66 (13.0%) episodes after two infusions. For 24 bleeding episodes (4.7%), five or more infusions were required; these 24 bleeding episodes were predominantly related to trauma, target joints, or muscle bleeds.

Hemostatic efficacy to resolve a bleed was rated by subjects as excellent or good in 84% of treated bleeding episodes. Excellent was defined as a dramatic response with abrupt pain relief and clear reduction in joint or hemorrhage site size, and good was defined as pain relief or reduction in hemorrhage size that may have required an additional infusion for resolution.

PTP < 12 years of age

There were 52 bleeding episodes; nine did not require treatment and resolved with IXINITY routine prophylaxis once or twice-weekly treatment. In 45 of 52 (86.5%) of the episodes, hemostasis was achieved with zero to two infusions. For four bleeding episodes (7.7%) three infusions were required, two episodes (3.8%) four infusions were required, and one episode (1.9%) required five infusions for resolution.

Hemostatic efficacy to resolve a bleed was rated by subjects as excellent or good in 41 (95%) of the 43 bleeding episodes that required treatment; two bleeding episodes did not have efficacy assessments. Excellent was defined as a dramatic response with abrupt pain relief and clear reduction in joint or bleeding site size and good was defined as pain relief or reduction in bleeding site size that may have required an additional infusion for resolution.

Perioperative Management

The efficacy analysis of IXINITY in perioperative management included 19 major surgeries performed in 16 male PTPs between 12 and 56 years of age (female carrier not included in efficacy analysis). Efficacy of IXINITY for support of major surgery was based on the surgeon’s assessment of efficacy including: a) at the time of surgery as estimation of blood loss as ‘less than expected’, ‘expected’, or ‘more than expected’; and b) at 12 and 24 hours post-surgical assessments of hemostasis as ‘adequate’, ‘better than adequate’, or ‘poorly controlled’. Transfusion requirements to support surgery were also monitored. There were no transfusions required during the procedures.

IXINITY was administered during major surgical procedures as bolus (n = 13) or continuous infusion (n = 6). IXINITY was rated as adequate or better in controlling hemostasis post-surgery as assessed by the surgeon when used in various procedures, including, knee arthroplasty (n = 8), elbow arthroplasty (n = 2), knee amputation (n = 1), percutaneous Achilles tendon lengthening (n = 1), open inguinal hernia repair (n = 1), tibiotalar fusion (n = 1), arthroscopic synovectomy (n = 2), and debridement (ankle, knee) (n = 3). In all instances, blood loss at surgery was ‘expected’ or ‘less than expected’ as assessed by the surgeon.

15 REFERENCES

1. Srivastava A, et al. World Federation of Hemophilia, Guidelines for the management of hemophilia. Haemophilia. 2013; 19(1):e1–e47.
2. Ingerslev J, Christiansen K, Ravn HB, et al. Antibodies to heterologous proteins in hemophilia A patients receiving recombinant factor VIII (Recombinate™). Thromb Haemost. 2002; 87:626–634.

16 HOW SUPPLIED/STORAGE AND HANDLING

IXINITY is supplied as a lyophilized powder in single-dose glass vials containing the labeled amount of factor IX activity, expressed in international units (IU). The actual factor IX activity in IU is stated on the label of each vial.

Kits include one single-dose vial (containing nominally 250, 500, 1000, 1500, 2000, or 3000 IU per vial), a 10 mL syringe pre-filled with 5 mL of Sterile Water for Injection with plunger rod attached, and a vial adapter with filter. None of the kit components are made with natural rubber latex.

Color Code | Nominal Strength | Kit NDC Number
Yellow | 250 IU | 59137-287-05
Blue | 500 IU | 59137-282-05
Green | 1000 IU | 59137-283-05
Orange | 1500 IU | 59137-284-05
Red | 2000 IU | 59137-288-05
Brown | 3000 IU | 59137-289-05

250 IU strength only; store at 2 to 8°C (36 to 46°F).

500, 1000, 1500, 2000, and 3000 IU strengths: store at 2 to 25°C (36 to 77°F).

Do not freeze.

Keep the vial in the carton and protect from light.

Infuse reconstituted solution immediately or within 3 hours of storage at room temperature after reconstitution. Do not refrigerate after reconstitution.

17 PATIENT COUNSELING INFORMATION

- Advise patients to read the FDA-approved patient labeling (Patient Information and Instructions for Use).
- Inform patients of the early signs of hypersensitivity reactions (including hives, generalized urticaria, chest tightness, wheezing, and hypotension) and anaphylaxis. Instruct patients to discontinue use of the product and contact their physician if these symptoms occur.
- Advise patients to contact their physician or treatment facility for further treatment and/or assessment if they experience a lack of clinical response to factor IX replacement therapy, as in some cases this may be a manifestation of an inhibitor.

Manufactured by:
Medexus Pharma, Inc.
Chicago, IL 60606
U.S. License No. 2220

Patient Information

IXINITY® [coagulation factor IX (recombinant)]

This leaflet summarizes important information about IXINITY. Please read it carefully before using this medicine. This information does not take the place of talking with your healthcare provider, and it does not include all of the important information about IXINITY. If you have any questions after reading this, ask your healthcare provider.

What is IXINITY?

IXINITY is a medicine used to replace clotting factor (factor IX) that is missing in people with hemophilia B. Hemophilia B is also called congenital factor IX deficiency or Christmas disease. Hemophilia B is an inherited bleeding disorder that prevents clotting.

Your healthcare provider may give you IXINITY when you have surgery.

Who should not use IXINITY?

You should not use IXINITY if you:

- Are allergic to hamsters
- Are allergic to any ingredients in IXINITY

Tell your healthcare provider if you are pregnant or breastfeeding because IXINITY may not be right for you.

What should I tell my healthcare provider before using IXINITY?

You should tell your healthcare provider if you:

- Have or have had any medical problems
- Take any medicines, including prescription and non-prescription medicines, such as over-the-counter medicines, supplements, or herbal remedies
- Have any allergies, including allergies to hamsters
- Are breastfeeding. It is not known if IXINITY passes into your milk and if it can harm your baby
- Are pregnant or planning to become pregnant. It is not known if IXINITY may harm your baby
- Have been told that you have inhibitors to factor IX (because IXINITY may not work for you)

How should I infuse IXINITY?

IXINITY is given directly into the bloodstream. IXINITY should be administered as ordered by your healthcare provider. You should be trained on how to do infusions by your healthcare provider or hemophilia treatment center. Many people with hemophilia B learn to infuse their IXINITY by themselves or with the help of a family member.

See the step-by-step guide (Instructions for Use) provided at the end of this leaflet.

Your healthcare provider will tell you how much IXINITY to use based on your weight, the severity of you hemophilia B, and where you are bleeding. You may have to have blood tests done after getting IXINITY to be sure that your blood level of factor IX is high enough to stop the bleeding. Call you healthcare provider right away if your bleeding does not stop after taking IXINITY.

What are the possible side effects of IXINITY?

Allergic reactions may occur with IXINITY. Call your healthcare provider or get emergency treatment right away if you get any of the following symptoms: rash, hives, itching, tightness of the throat, chest pain or tightness, difficulty breathing, light-headedness, dizziness, nausea, or fainting.

Tell your healthcare provider about any side effect that bothers you or does not go away.

The most common side effect of IXINITY in clinical trials was headache.

These are not all the side effects possible with IXINITY. You can ask your healthcare provider for information that is written for healthcare professionals.

Call your healthcare provider for medical advice about side effects. You may report side effects to the FDA at 1-800-FDA-1088.

What are the IXINITY dosage strengths?

IXINITY comes in vials containing six different dosage strengths: 250, 500, 1000, 1500, 2000 and 3000 international units (IU). The actual strength will be printed on the label of the vial and on the box. The six different strengths in the vials are color coded as follows:

Color Code | Nominal Strength
Yellow | 250 IU
Blue | 500 IU
Green | 1000 IU
Orange | 1500 IU
Red | 2000 IU
Brown | 3000 IU

Always check the actual dosage strength printed on the label to make sure you are using the strength prescribed by your healthcare provider.

How should I store IXINITY?

250 IU strength only; store at 2 to 8°C (36 to 46°F). Do not freeze.

500, 1000, 1500, 2000, and 3000 IU strengths; store at 2 to 25°C (36 to 77°F). Do not freeze.

Do not use IXINITY after the expiration date printed on the label. Throw away any unused IXINITY and diluents after it reaches this date.

Reconstituted product (after mixing dry product with Sterile Water for Injection) must be used within 3 hours and cannot be stored or refrigerated. Discard any IXINITY left in the vial at the end of your infusion.

What else should I know about IXINITY?

Your body may form inhibitors to factor IX. An inhibitor is part of the body’s immune system. If you form inhibitors, it may stop IXINITY from working properly. Consult with your healthcare provider to make sure you are carefully monitored with blood tests to check for the development of inhibitors to factor IX. Consult your doctor promptly if bleeding is not controlled with IXINITY as expected.

Medicines are sometimes prescribed for purposes other than those listed here. Do not use IXINITY for a condition for which it is not prescribed. Do not share IXINITY with other people, even if they have the same symptoms as you.

Resources available to patients

For information on patient assistance programs that may be available to you, please call our IXINITY Patient Care Center at 1-855-IXINITY (1-855-494-6489).

Manufactured by:
Medexus Pharma, Inc.
Chicago, IL 60606
U.S. License No. 2220

Instructions for Use

IXINITY [coagulation factor IX (recombinant)]

For intravenous use after reconstitution only

Do not attempt to do an infusion to yourself unless you have been taught how by your healthcare provider or hemophilia center.

Always follow the specific instructions given by your healthcare provider. The steps listed below are general guidelines for using IXINITY. If you are unsure of the procedures, please call your healthcare provider before using IXINITY. Your healthcare provider will prescribe the dose that you should take.

Before starting reconstitution and administration you will need the following items that are included in each kit of IXINITY:

- One (or more) vial(s) of IXINITY 250, 500, 1000, 1500, 2000, or 3000 IU powder, as prescribed by your healthcare provider
- One (or more) 10 mL syringe(s), pre-filled with 5 mL of Sterile Water for Injection (pre-filled syringe) with plunger rod attached
- Sterile vial adapter with filter

In addition, you will need the following items that are not included in the kit:

- One sterile LUER-LOK syringe (administration syringe); additional or larger syringes may be required if pooling multiple vials
- Sterile alcohol swabs
- Sterile infusion set
- Sterile gauze pad
- Sterile bandage

IXINITY is supplied in kits that include single-dose vials which contain vials of IXINITY (250, 500, 1000, 1500, 2000, or 3000 IU of powder), a 10 mL syringe pre-filled with 5 mL of Sterile Water for Injection with plunger rod attached (to be used for reconstitution only), and a sterile vial adapter with filter.

RECONSTITUTION INSTRUCTIONS

Wash your hands and then clean a flat area before starting the steps for reconstituting IXINITY. Use an aseptic technique during reconstitution.

1. Remove the pre-filled syringe and IXINITY vial from storage and allow them to reach room temperature before use. Check the expiration date on the IXINITY vial.

2. Remove the plastic cap from the IXINITY vial and place the vial top up on the clean surface. You will see a rubber circle on the top of the vial.

3. Wipe the top of the IXINITY vial with a sterile alcohol swab and allow it to dry. After cleaning, do not touch the rubber circle with your hands or allow it to touch another object.

4. Peel back the paper cover of the vial adapter package. Be careful not to touch the LUER-LOK (tip) in the center of the vial adapter. Do not remove the adapter from the package.

5. Leave the vial adapter in the package and place it open end up on the clean surface with the LUER-LOK pointing up.

6. Twist off the tip cap counterclockwise from the pre-filled syringe. Do not touch the inside of the cap or the syringe tip.

7. While firmly holding the package containing the adapter with one hand and the barrel of the pre-filled syringe with the other, connect the pre-filled syringe to the vial adapter by pushing the syringe tip down onto the LUER-LOK in the center of the vial adapter, turning clockwise until the syringe is secured.

8. Carefully lift up the combined syringe-and-vial-adapter and remove it from the plastic package and discard packaging.

9. With one hand, continue to hold the combined syringe-and-vial-adapter. With the other hand, hold the IXINITY vial tightly on the clean, flat surface. Do not touch the top of the IXINITY vial or the filter spike of the combined syringe and vial adapter.

10. Place the vial adapter over the IXINITY vial on the table; firmly push the filter spike of the vial adapter through the center of the IXINITY vial rubber circle until the clear plastic cap snaps onto the IXINITY vial.

11. Slowly push the plunger rod down to transfer all of the liquid from the syringe into the IXINITY vial.

- With the syringe and the vial still attached, gently swirl, in a circular motion, the IXINITY vial until the product is fully dissolved. IXINITY is a clear, colorless solution without visible particles. Inspect the final solution for specks before administration. Do not use contents of vial if specks or particles persist after proper reconstitution.

12. NOTE: If you use more than one vial of IXINITY per infusion, reconstitute each vial as per the previous instructions.

13. Remove the diluent syringe from the vial adapter by turning syringe counterclockwise until it is completely detached. Do not touch the luer tip of the vial adapter.

14. Remove the LUER-LOK syringe (administration syringe) from its sterile packaging, taking care to not touch the luer tip of the syringe. Attach to the reconstituted vial and vial adapter by turning syringe clockwise until it is securely attached.

15. Press and keep the plunger down and turn the IXINITY vial/vial adapter/administration syringe upside down to transfer the solution. Draw up the solution into the administration syringe slowly until all solution is transferred into the syringe. Inspect the vial to confirm as much liquid as possible has been extracted into the administration syringe. NOTE: If you use more than one vial of IXINITY per infusion, extract reconstituted liquid from each vial, as per the previous instructions.

16. Hold onto the vial adapter with one hand and firmly grasp the administration syringe with the other and unscrew the administration syringe from the vial adapter turning either counterclockwise. Do not touch the tip of the syringe to any object or surface. NOTE: If multiple reconstituted vials are required for infusion, do not detach the large LUER-LOK administration syringe from the first vial until you are ready to attach the next vial (with vial adapter attached).

17. Prior to administering the solution, invert the administration syringe so that the tip is pointed toward the ceiling and express any air in the syringe. Place the administration syringe containing the IXINITY solution on the clean surface, making sure that the tip does not touch anything.

The reconstituted solution should be infused immediately or within 3 hours of storage at room temperature after reconstitution. NOTE: The luer tip of the syringe must not be touched by any objects or surfaces, when disconnecting the syringe from the vial adapter, and when transferring the administration syringe to the infusion set.

If you are using more than one vial, stop here and proceed to the Pooling Instructions.

POOLING INSTRUCTIONS

POOLING is the process of combining two or more reconstituted vials into a larger administration syringe prior to intravenous administration.

Do not detach the large LUER-LOK administration syringe until you are ready to attach the next vial (with vial adapter attached).

Follow the instructions above for reconstitution of the second vial.

1. Remove the administration syringe from the first vial adapter by turning it counterclockwise until it is completely detached.
2. Attach the administration syringe to the second reconstituted vial by turning clockwise until it is securely attached.
3. Turn the IXINITY vial/vial adapter/administration syringe upside down, slowly pull on the plunger rod to draw the solution into the administration syringe (see Step 15 above).

Repeat this POOLING procedure with each vial you will be using.

Once you have pooled the required dose, proceed to administration using the administration syringe.

ADMINISTRATION INSTRUCTIONS

For intravenous use after reconstitution only.

IXINITY is administered by intravenous (IV) infusion after reconstitution with diluent (Sterile Water for Injection) supplied in the pre-filled syringe.

IXINITY must not be mixed with other medicinal products for infusion.

Reconstituted IXINITY must be pulled into an administration syringe prior to infusion.

IXINITY is normally administered intravenously over about 5 minutes at a maximum infusion rate of 10 mL per minute. The infusion rate should be adapted to the comfort level of each patient.

1. Attach the administration syringe containing the reconstituted IXINITY solution to the luer end of the sterile infusion set. Inspect for and remove any air bubbles in the infusion set and administration syringe. NOTE: The luer tip of the administration syringe and the luer connection of the infusion set must not be touched by any object or surface, prior to connection of the administration syringe.
2. Transfer IXINITY solution into the tube by pressing the syringe plunger until the tubing is completely filled. Once again, inspect for and remove any air bubbles in the infusion set and administration syringe.
3. Perform venipuncture as directed by your healthcare provider.
4. Limit the amount of blood entering the tubing. Blood must never enter the syringe. If blood is observed in the tubing or syringe, discard all material and resume administration with a new package.
5. Following completion of the infusion, remove the infusion set, press the sterile gauze on the infusion site until bleeding has stopped, then apply a sterile bandage. The amount of drug product remaining in the infusion set should be minimal. Log the batch number of the IXINITY used; it is located on the container.

Dispose of all unused solution, empty vials, and used needles and syringes in an appropriate container for throwing away medical waste as it may hurt others if not handled properly.

Contact your healthcare provider or local hemophilia treatment center if you experience any problems.

IXINITY® coagulation factor IX (recombinant) and any and all Medexus Pharma, Inc. brand, product, service and feature names, logos, and slogans are trademarks or registered trademarks of Medexus Pharma, Inc. in the United States or other countries. All rights reserved.

LUER-LOK™ is a trademark of Becton, Dickinson and Company. All other brand, product, service and feature names or trademarks are the property of their respective owners.

Manufactured by:
Medexus Pharma, Inc.
Chicago, IL 60606
U.S. License No. 2220